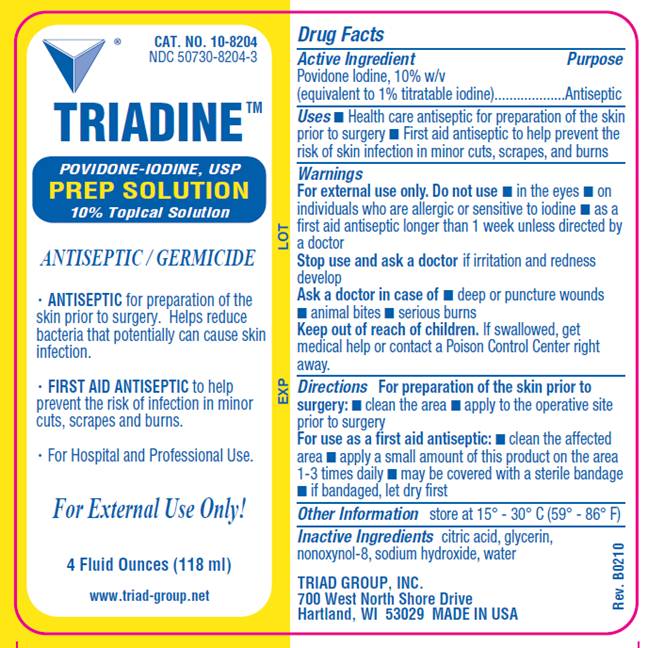 DRUG LABEL: Triadine Prep
NDC: 50730-8204 | Form: SOLUTION
Manufacturer: Triad Group
Category: otc | Type: HUMAN OTC DRUG LABEL
Date: 20100419

ACTIVE INGREDIENTS: povidone-iodine .10 mg/1 mL
INACTIVE INGREDIENTS: citric acid monohydrate; glycerin; sodium hydroxide; water

DRUG FACTS

ACTIVE INGREDIENT

Povidone Iodine,10% w/v (equivalent to 1% titratable iodine)

PURPOSE

Antiseptic

USES

- Health-care antiseptic for preparation of the skin prior to surgery
- First id antiseptic to help prevent the risk of infection in minor cuts, scrapes and burns.

WARNINGS

For external use only.

Do not use

- in the eyes
- on individuals who are allergic or sensitive to iodine
- as a first aid antiseptic for longer than 1 week

Ask a doctor in case of

- deep or puncture wounds
- animal bites
- serious burns

Stop use and ask a doctor

- if irritation and redness develop

Keep out of reach of children

If swallowed, get medical help or contact a Poison Control Center right away.

DIRECTIONS

For preparation of the skin prior to surgery:

- clean the area
- apply to the operative site prior to surgery

As a first aid antiseptic

- clean the affected area
- apply a small amount of this product to the area 1-3 times daily
- may be covered with a sterile bandage
- if bandaged, let dry first

OTHER INFORMATION

store at 15° - 30° C (59° - 86° F)

INACTIVE INGREDIENTS

citric acid, glycerin, nonoxynol-8, sodium hydroxide, water

LABEL INFORMATION

Cat. No. 10-8204
NDC 50730-8204-4
TRIADINE™

POVIDONE-IODINE, USP
PREP SOLUTION
10% Topical Solution
ANTISEPTIC / GERMICIDE

- ANTISEPTIC for preparation of the skin prior to surgery. Helps reduce bacteria that potentially can cause skin infection.
- FIRST AID ANTISEPTIC to help prevent the risk of infection in minor cuts, scrapes and burns.
- For Hospital and Professional Use.

For External Use Only!
4 Fluid Ounces (118 ml)

www.triad-group.net

TRIAD GROUP, INC.
700 West North Shore Drive
Hartland, WI 53029 MADE IN USA